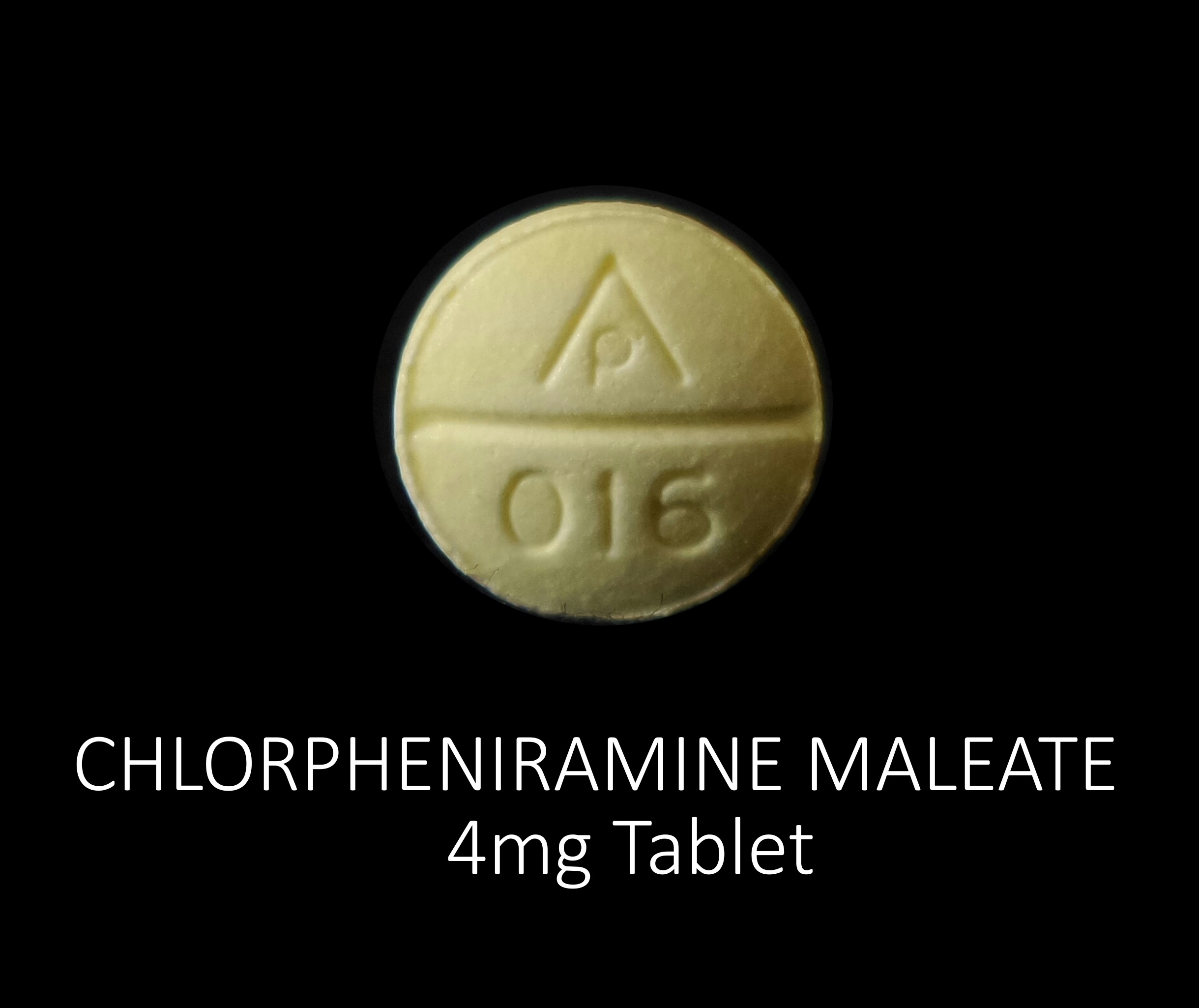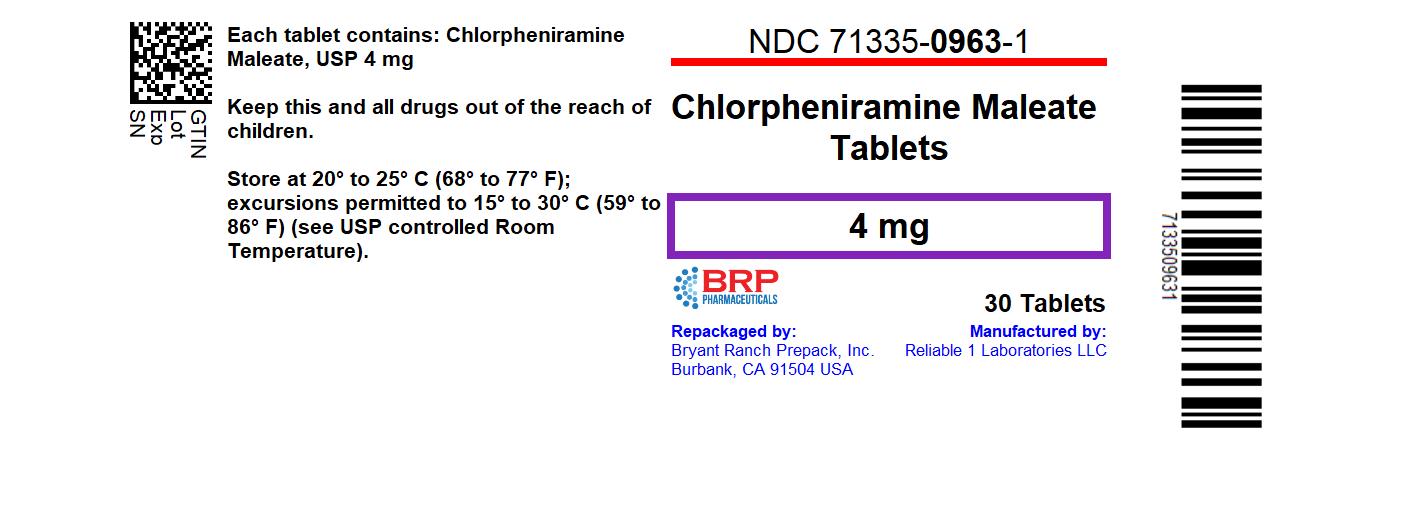 DRUG LABEL: Chlorpheniramine Maleate 4 mg
NDC: 71335-0963 | Form: TABLET
Manufacturer: Bryant Ranch Prepack
Category: otc | Type: HUMAN OTC DRUG LABEL
Date: 20240517

ACTIVE INGREDIENTS: CHLORPHENIRAMINE MALEATE 4 mg/1 1
INACTIVE INGREDIENTS: D&C YELLOW NO. 10; CROSCARMELLOSE SODIUM; ANHYDROUS DIBASIC CALCIUM PHOSPHATE; MAGNESIUM STEARATE; MICROCRYSTALLINE CELLULOSE; STARCH, CORN; SILICON DIOXIDE

Chlorpheniramine Maleate 4 mg

Drug Facts

Active ingredient (in each tablet)

Chlorpheniramine maleate 4 mg

Purpose

Antihistamine

Warnings

Ask a doctor before use if you have

- glaucoma
- trouble urinating due to enlarged prostate gland
- a breathing problem such as emphysema or chronic bronchitis

Ask a doctor or pharmacist before use if you are taking sedatives or tranquilizers

When using this product

- you may get drowsy
- avoid alcoholic drinks
- alcohol, sedatives and tranquilizers may increase drowsiness
- be careful when driving a motor vehicle or operating machinery
- excitability may occur, especially in children

Drug Facts continued on back of label

PREGNANCY OR BREAST FEEDING

If pregnant or breast-feeding, ask a health professional before use.

Keep out of reach of children. In case of overdose, get medical help or contact a Poison Control Center right away.

Directions

adults and children 12 years and over | take 1 tablet every 4 to 6 hours, not more than 6 tablets in 24 hours
children 6 years to under 12 years | take 1/2 tablet every 4 to 6 hours, not more than 3 tablets in 24 hours
children under 6 years | do not use

Other information

- each tablet contains: calsium 40 mg
- store at 15°-30°C (59°-86°F)

Inactive ingredients

croscarmellose sodium, D&C yellow# 10 (Al-lake), dicalcium phosphate, magnesium stearate, microcrystalline cellulose, pregelatinized starch, silicon dioxide

Questions or comments?

call 516-341-0666, 8:30 am - 4:30 pm ET, Monday - Friday

TAMPER EVIDENT: DO NOT USE IF IMPRINTED SAFETY SEAL UNDER CAP IS BROKEN OR MISSING

* Reliable 1 Laboratories LLC is not affiliated with the owner of the trademark Chlor-Trimeton®

Distributed by: Reliable 1 Laboratories LLC, Valley Stream, NY 11580

www.reliable1labs.com

Uses

temporarily relieves these symptoms of hay fever or other upper respiratory allergies:

- runny nose
- sneezing
- itchy nose or throat
- itchy, watery eyes

HOW SUPPLIED

NDC: 71335-0963-1: 30 Tablets in a BOTTLE

NDC: 71335-0963-2: 60 Tablets in a BOTTLE

NDC: 71335-0963-3: 100 Tablets in a BOTTLE

NDC: 71335-0963-4: 120 Tablets in a BOTTLE

NDC: 71335-0963-5: 40 Tablets in a BOTTLE

NDC: 71335-0963-6: 24 Tablets in a BOTTLE

Repackaged/Relabeled by:
Bryant Ranch Prepack, Inc.
Burbank, CA 91504

PACKAGE LABEL

Chlorpheniramine Maleate 4 mg Tablet